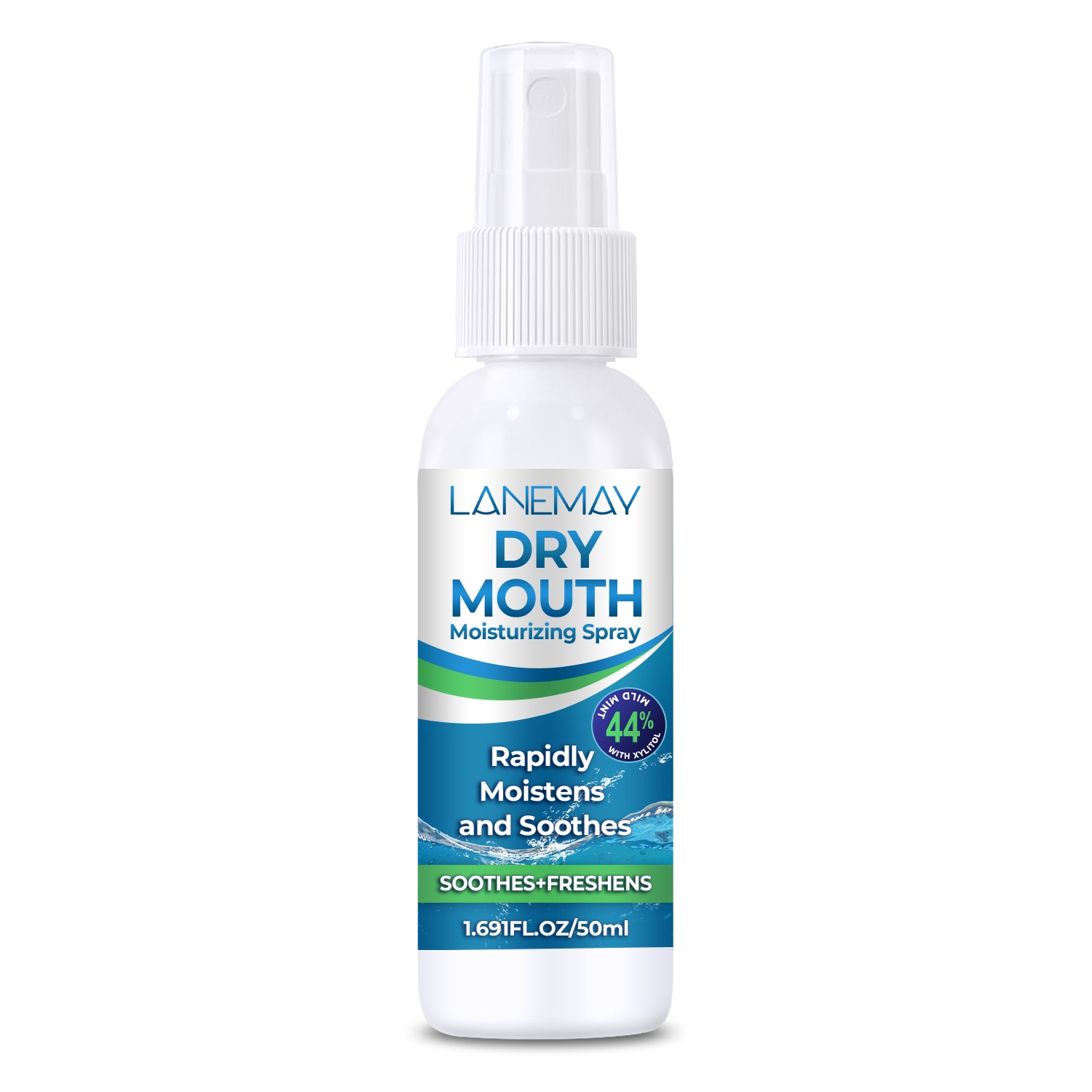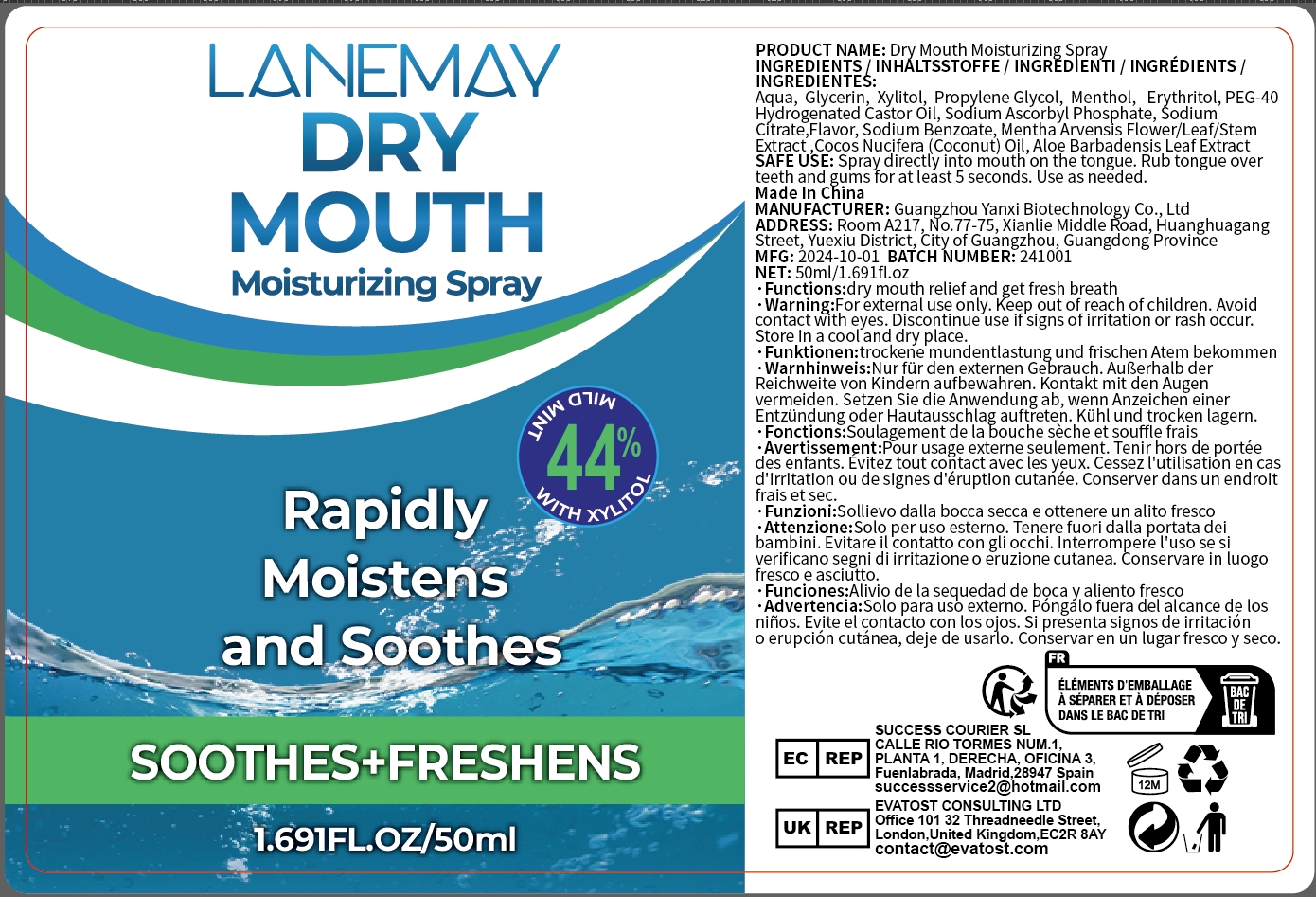 DRUG LABEL: dry mouth moisturizingspray
NDC: 84025-267 | Form: LIQUID
Manufacturer: Guangzhou Yanxi Biotechnology Co., Ltd
Category: otc | Type: HUMAN OTC DRUG LABEL
Date: 20241122

ACTIVE INGREDIENTS: MENTHOL 2 mg/50 mL; XYLITOL 3 mg/50 mL
INACTIVE INGREDIENTS: WATER

DOSAGE AND ADMINISTRATION

Spray directly into mouth on the tongue.Rub tongue over teeth and gums for at least 5 seconds.Use as needed.

WARNINGS

Keep out of children

INACTIVE INGREDIENT

Aqua

INDICATIONS AND USAGE

For daily oral care

Keep out of children

PURPOSE

Rapidlyl, moistens and soothes